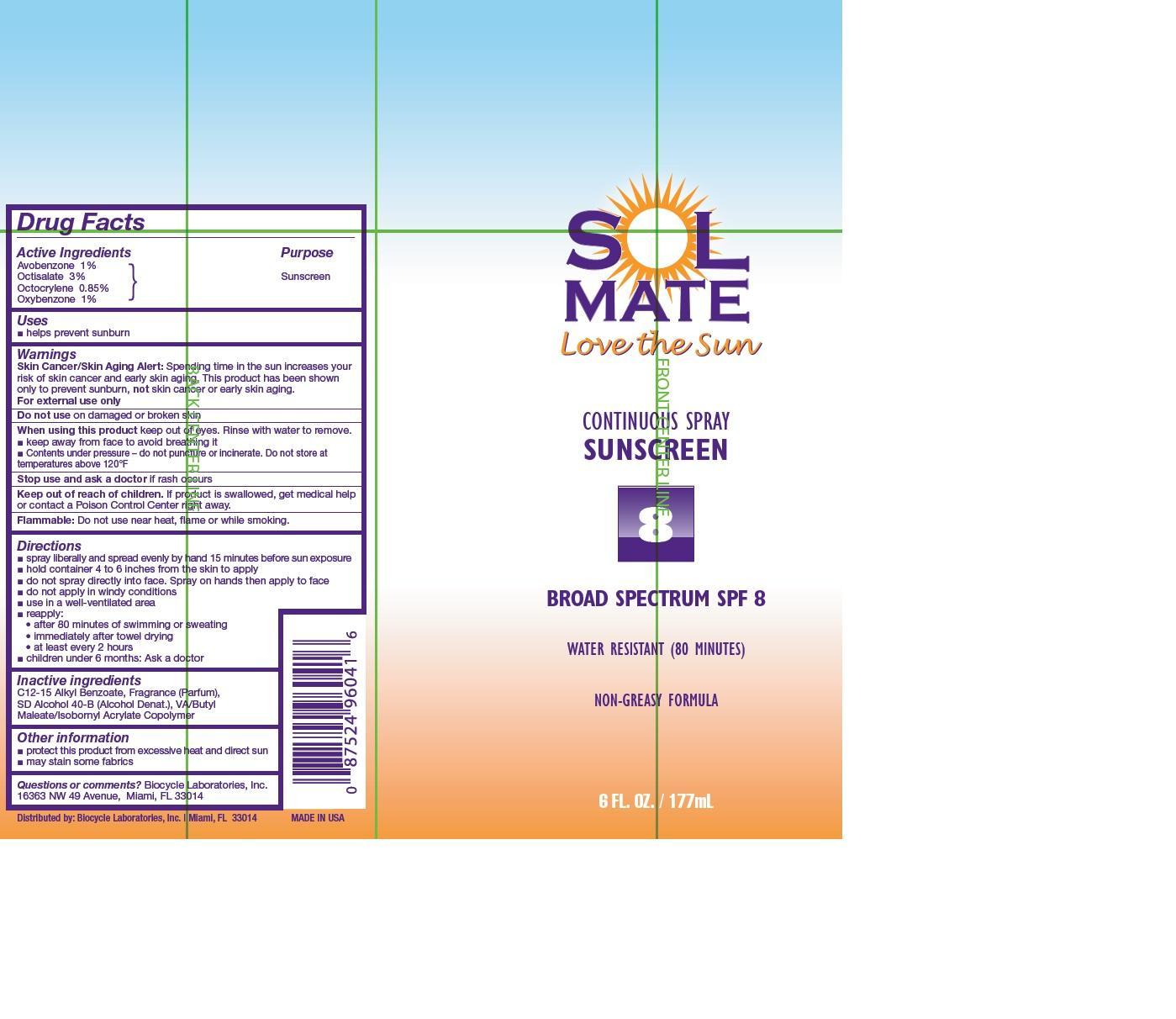 DRUG LABEL: SolMate
NDC: 13630-0075 | Form: AEROSOL, SPRAY
Manufacturer: Prime Packaging, Inc.
Category: otc | Type: HUMAN OTC DRUG LABEL
Date: 20200117

ACTIVE INGREDIENTS: AVOBENZONE 8.1 mg/1 mL; OCTISALATE 24.3 mg/1 mL; OCTOCRYLENE 6.885 mg/1 mL; OXYBENZONE 8.1 mg/1 mL
INACTIVE INGREDIENTS: ALKYL (C12-15) BENZOATE; ALCOHOL; BUTYL MALEURATE; ISOBORNYL ACRYLATE

Active ingredients

Avobenzone 1 %, Octisalate 3 %, Octocrylene 0.85 %, and Oxybenzone 1 %

Purpose

Sunscreen

Uses

- helps prevent sunburn

Warnings

OTHER SAFETY INFORMATION

Skin Cancer/Skin Aging Alert: Spending time in the sun increases your risk of skin cancer skin aging. This product has been shown only to prevent sunburn, not skin cancer or early skin aging.

For external use only

Do not use on damaged or broken skin

When using this product keep out of eyes. Rinse with water to remove.

•Keep away from face to avoid breathing it.

•Contents under pressure-do not puncture or incinerate. Do not store at temperatures above 120°F

Stop use and ask a doctor if rash occurs

Keep out of reach of children. If product is swallowed, get medical help or contact a Poison Control Center right away.

OTHER SAFETY INFORMATION

Flammable: Do not use near heat, flame or while smoking.

Directions

- spray liberally and spread evenly by hand 15 minutes before sun exposure
- hold container 4 to 6 inches from the skin to apply
- do not spray directly into face. Spray on hands then apply to face.
- do not apply in windy conditions
- use in a well-ventilated area
- reapply:
- After 80 minutes of swimming or sweating
- immediately after towel drying
- at least every 2 hours
- children under 6 months: Ask a doctor

Inactive Ingredients

C12-15 Alkyl Benzoate, Fragrance (Parfum), SD Alcohol 40-B (Alcohol Denat.), VA/Butyl Maleate/Isobornyl Acrylate Copolymer

Other Information

•protect this product from excessive heat and direct sun

•may stain fabrics.

Questions or comments? Biocycle Laboratories, Inc.

16363 NW 49 Avenue, Miami, Fl 33014

PRINCIPAL DISPLAY PANEL - 177 mL Can Label

SOL

MATE

Love the Sun

Continuous Spray

Sunscreen

8

Broad Spectrum SPF 8

Water Resistant (80) Minutes

Non-Greasy Formula